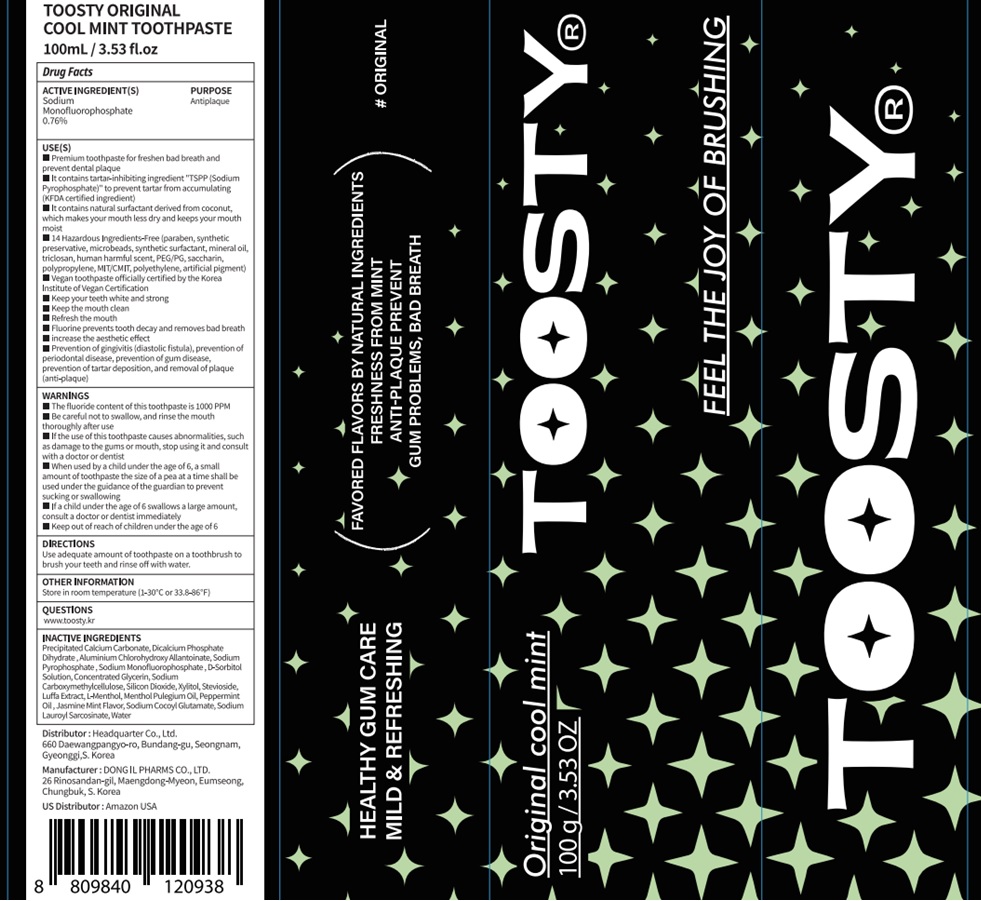 DRUG LABEL: Toosty Original Cool Mint Toothpaste
NDC: 82662-060 | Form: PASTE, DENTIFRICE
Manufacturer: Headquarter Co., Ltd
Category: otc | Type: HUMAN OTC DRUG LABEL
Date: 20240119

ACTIVE INGREDIENTS: Sodium Monofluorophosphate 0.76 g/100 g
INACTIVE INGREDIENTS: Calcium Carbonate; ANHYDROUS DIBASIC CALCIUM PHOSPHATE; ALCLOXA

ACTIVE INGREDIENTS

Sodium Monofluorophosphate 0.76%

INACTIVE INGREDIENTS

Precipitated Calcium Carbonate, Dicalcium Phosphate Digydrated, Aluminium Chlorohydroxy Allantoinate, Sodium Pyrophosphate, Sodium Monofluorophosphate, D-Sorbitol Solution, Concentrated Glycerin, Sodium Carboxymethylcellulose, Silicon Dioxide, Xylitol, Stevioside, Lufa Extract, L-Menthol, Menthol Pulegium Oil, Peppermint Oil, Jasmine Mint Flavor, Sodium Cocoyl Glutamate, Sodium Lauroyl Sarcosinate, Water

PURPOSE

Antiplaque

WARNINGS

■ The fluoride content of this toothpaste is 1000 PPM
■ Be careful not to swallow, and rinse the mouth thoroughly after use
■ If the use of this toothpaste causes abnormalities, such as damage to the gums or mouth, stop using it and consult with a doctor or dentist
■ When used by a child under the age of 6, a small amount of toothpaste the size of a pea at a time shall be used under the guidance of the guardian to prevent sucking or swallowing
■ If a child under the age of 6 swallows a large amount, consult a doctor or dentist immediately
■ Keep out of reach of children under the age of 6

Keep out of reach of children under the age of 6

Uses

■ Premium toothpaste for freshen bad breath and prevent dental plaque
■ It contains tartar-inhibiting ingredient "TSPP (Sodium Pyrophosphate)" to prevent tartar from accumulating (KFDA certified ingredient)
■ It contains natural surfactant derived from coconut, which makes your mouth less dry and keeps your mouth moist
■ 14 Hazardous Ingredients-Free (paraben, synthetic preservative, microbeads, synthetic surfactant, mineral oil, triclosan, human harmful scent, PEG/PG, saccharin, polypropylene, MIT/CMIT, polyethylene, artificial pigment)
■ Vegan toothpaste officially certified by the Korea Institute of Vegan Certification
■ Keep your teeth white and strong
■ Keep the mouth clean
■ Refresh the mouth
■ Fluorine prevents tooth decay and removes bad breath
■ increase the aesthetic effect
■ Prevention of gingivitis (diastolic fistula), prevention of periodontal disease, prevention of gum disease, prevention of tartar deposition, and removal of plaque (anti-plaque)

Directions

■ Use adequate amount of toothpaste on a toothbrush to brush your teeth and rinse off with water.

Other Information

■ Store in room temperature (1-30℃ or 33.8-86℉)

Questions

■ www.toosty.kr